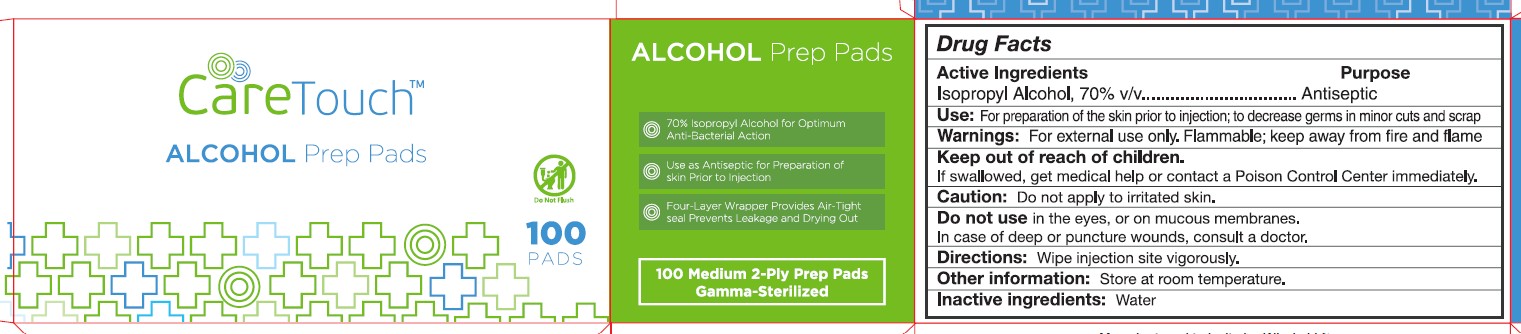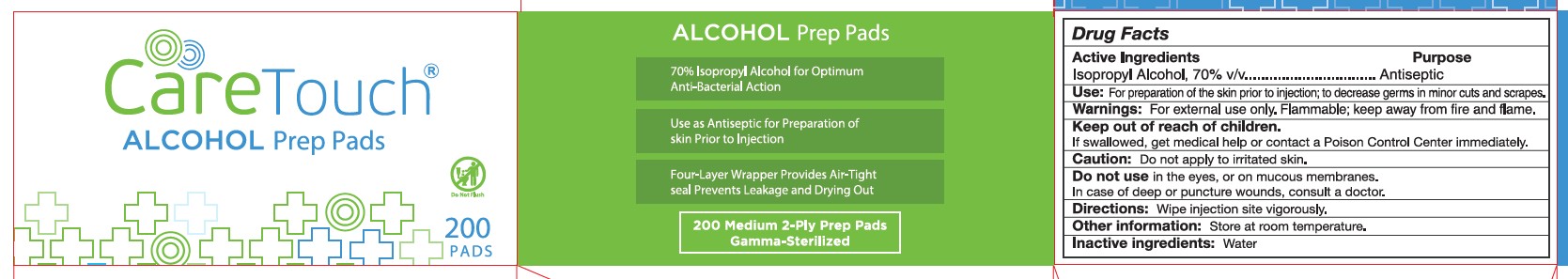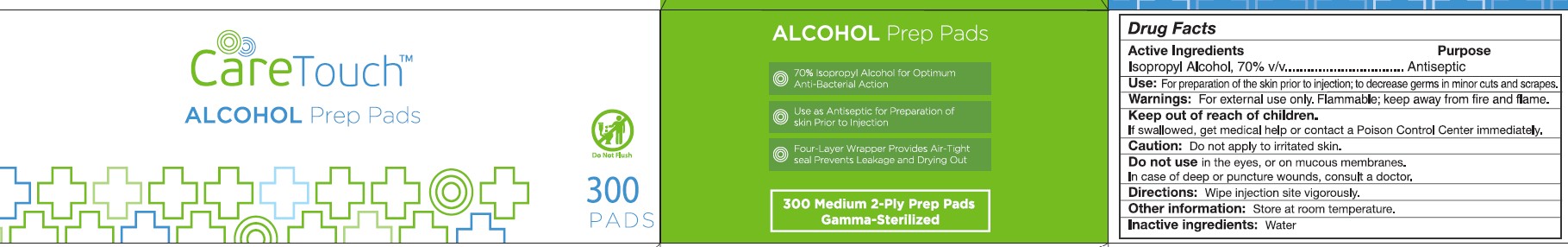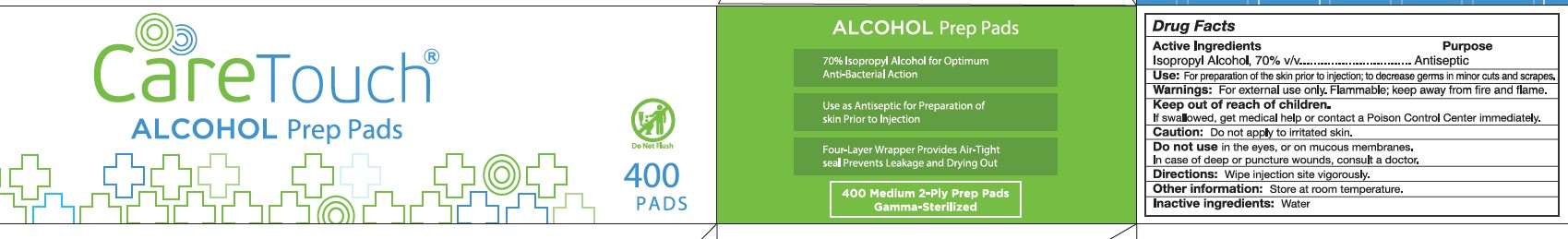 DRUG LABEL: Alcohol Prep Pads
NDC: 60913-025 | Form: SWAB
Manufacturer: Phoenix Healthcare Solutions LLC
Category: otc | Type: HUMAN OTC DRUG LABEL
Date: 20251023

ACTIVE INGREDIENTS: ISOPROPYL ALCOHOL 0.7 mL/1 mL
INACTIVE INGREDIENTS: WATER

Caretouch Alcohol Prep Pads (Whele LLC)

Active Ingredients

Isopropyl Alcohol 70% v/v

Purpose

Antiseptic

Use

For preparation of the Skinprior to injection, to decrease germs in minor cuts & scrap.

Warning

For External Use Only. Flammable, Keep away from fire & flame.

Keep out of reach of Children

If Swallowed, get medical help or contact a Poison Control Center Immediately.

Caution

Do not apply to irritated Skin

Do not use in the eyes, or on mucous membranes. In case of deep or puncture wounds, consult a doctor.

Directions

Wipe injection site Vigorously

Other Information

Store at Room Temperature

Inactive Ingredient

Water